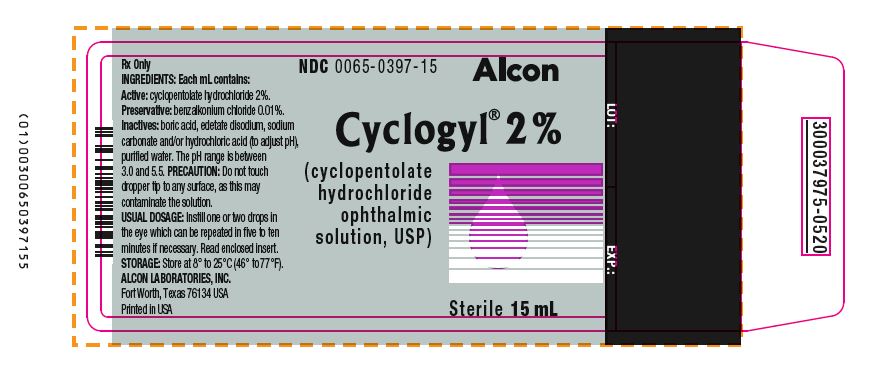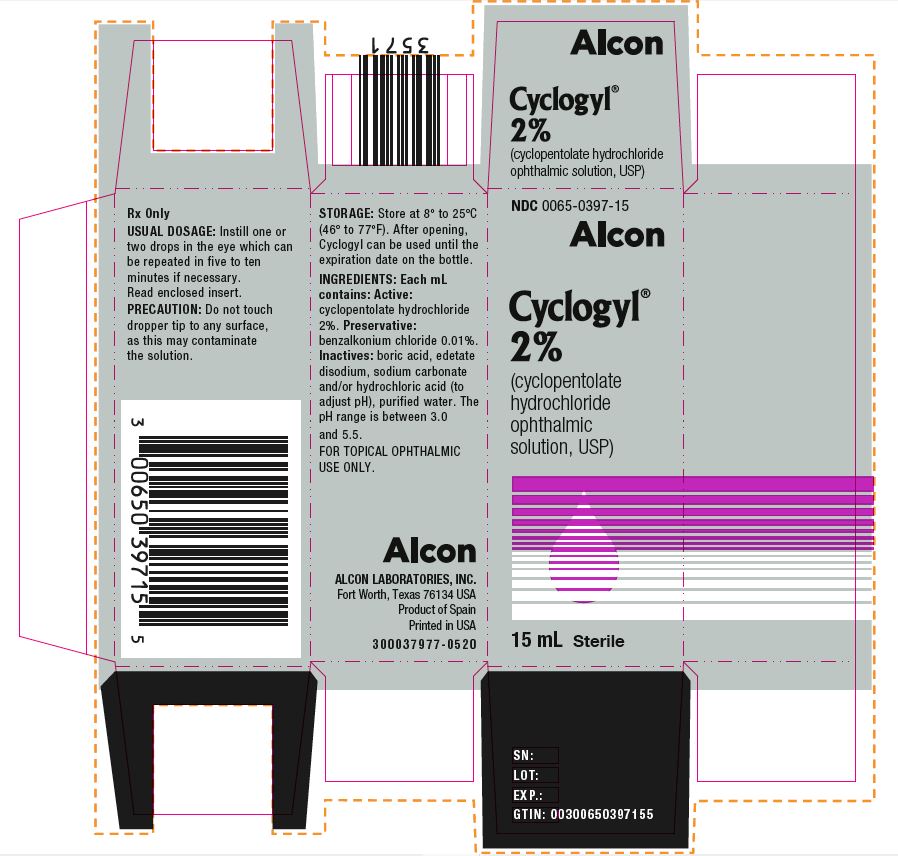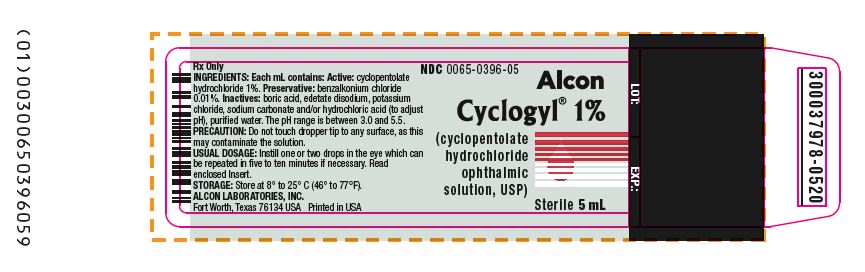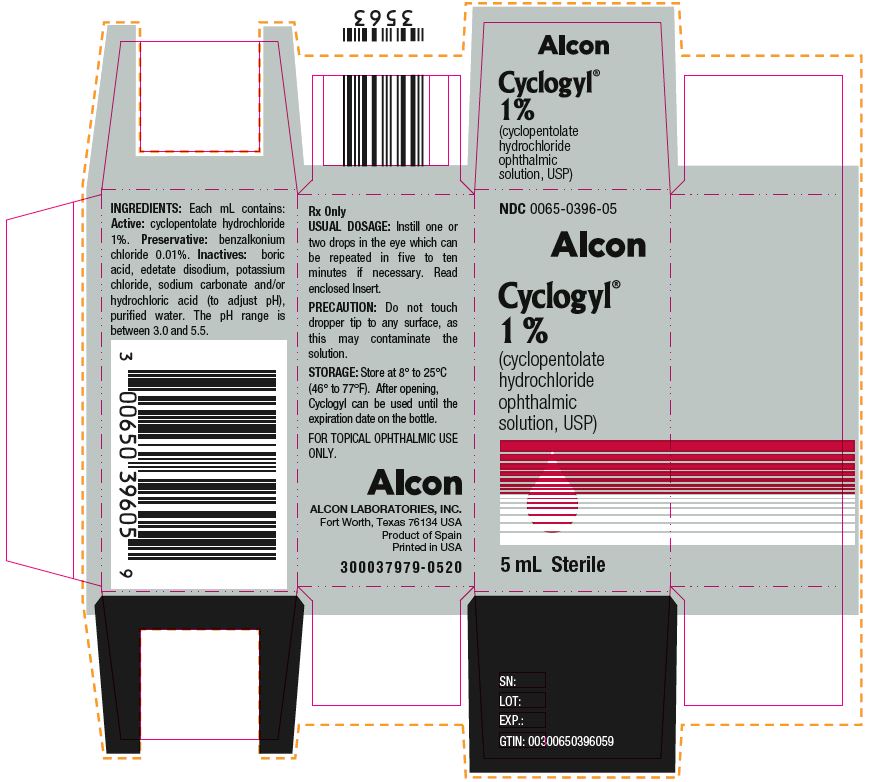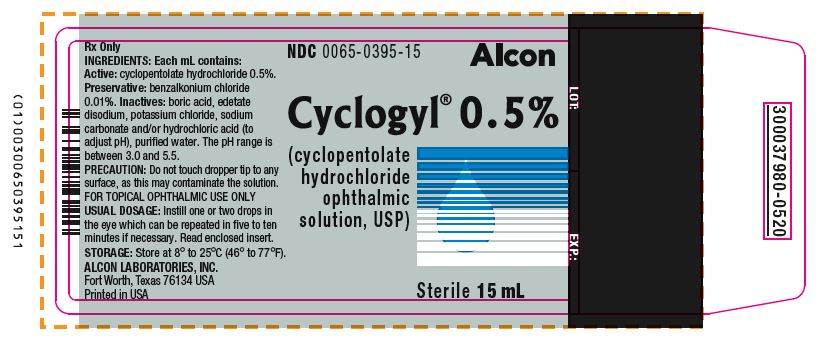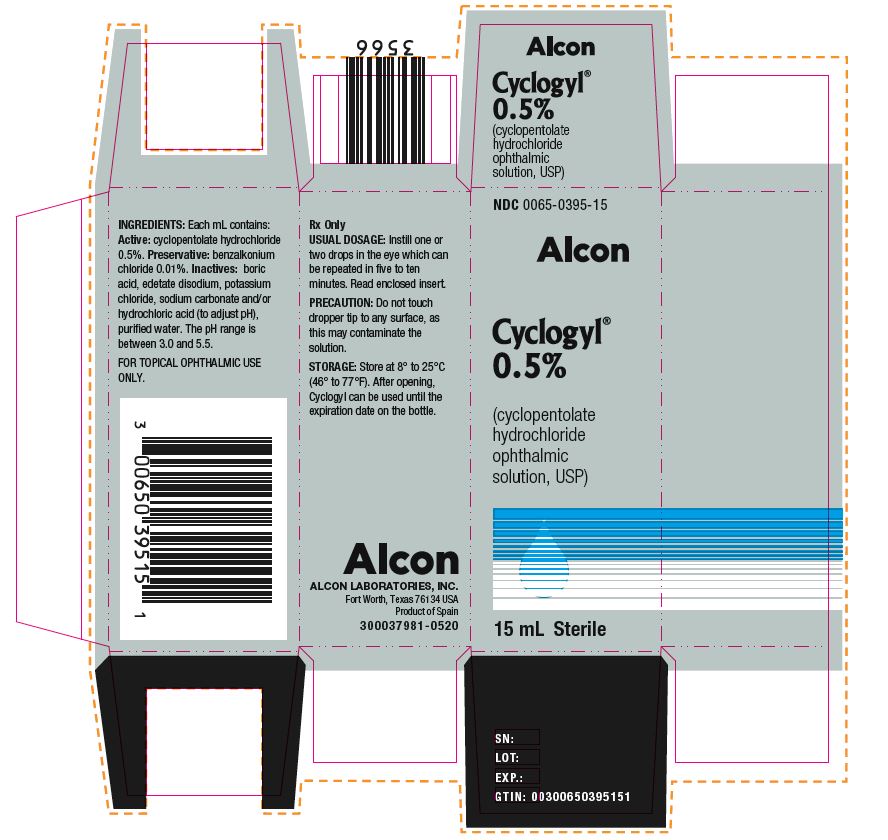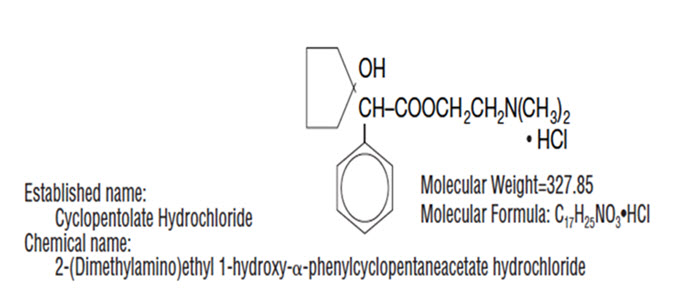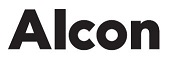 DRUG LABEL: Cyclogyl 
NDC: 0065-0395 | Form: SOLUTION/ DROPS
Manufacturer: Alcon Laboratories, Inc.
Category: prescription | Type: HUMAN PRESCRIPTION DRUG LABEL
Date: 20240625

ACTIVE INGREDIENTS: CYCLOPENTOLATE HYDROCHLORIDE 5 mg/1 mL
INACTIVE INGREDIENTS: BENZALKONIUM CHLORIDE; BORIC ACID; EDETATE DISODIUM; SODIUM CARBONATE; HYDROCHLORIC ACID; WATER; POTASSIUM CHLORIDE

CYCLOGYL®
(cyclopentolate hydrochloride ophthalmic solution, USP)

Rx Only

DESCRIPTION: CYCLOGYL® (cyclopentolate hydrochloride ophthalmic solution, USP) is an anticholinergic prepared as a sterile, borate buffered, solution for topical ocular use. It is supplied in three strengths. The active ingredient is represented by the structural formula:

Each mL of CYCLOGYL® (cyclopentolate hydrochloride ophthalmic solution, USP) contains: Active: cyclopentolate hydrochloride 0.5%, 1% or 2%. Preservative: benzalkonium chloride 0.01%. Inactives: boric acid, edetate disodium, potassium chloride (except 2% strength), sodium carbonate and/or hydrochloric acid (to adjust pH), purified water. The pH range is between 3.0 and 5.5.

CLINICAL PHARMACOLOGY

CLINICAL PHARMACOLOGY: This anticholinergic preparation blocks the responses of the sphincter muscle of the iris and the accommodative muscle of the ciliary body to cholinergic stimulation, producing pupillary dilation (mydriasis) and paralysis of accommodation (cycloplegia). It acts rapidly, but has a shorter duration than atropine. Maximal cycloplegia occurs within 25 to 75 minutes after instillation. Complete recovery of accommodation usually takes 6 to 24 hours. Complete recovery from mydriasis in some individuals may require several days. Heavily pigmented irides may require more doses than lightly pigmented irides.

INDICATIONS AND USAGE: Cyclopentolate hydrochloride is used to produce mydriasis and cycloplegia.

CONTRAINDICATIONS

CONTRAINDICATIONS: Should not be used if the patient is hypersensitive to any component of this preparation.

WARNINGS

WARNINGS: FOR TOPICAL OPHTHALMIC USE ONLY. NOT FOR INJECTION. This preparation may cause Central Nervous System (CNS) disturbances. This is especially true in younger age groups, but may occur at any age, especially with the stronger solutions. Infants are especially prone to CNS and cardiopulmonary side effects from cyclopentolate. To minimize absorption, use only 1 drop of 0.5% CYCLOGYL solution per eye, followed by pressure applied over the nasolacrimal sac for two to three minutes. Observe infants closely for at least 30 minutes following instillation.

Mydriatics may produce a transient elevation of intraocular pressure. Therefore, patients with untreated narrow angle glaucoma or anatomically narrow angles may be susceptible to angle closure following administration.

PRECAUTIONS:

GENERAL PRECAUTIONS

General: The lacrimal sac should be compressed by digital pressure for two to three minutes after instillation to reduce excessive systemic absorption. Caution should be observed when considering use of this medication in the presence of Down's syndrome.

PATIENT COUNSELING INFORMATION

Information for Patients: Do not touch dropper tip to any surface, as this may contaminate the solution. A transient burning sensation may occur upon instillation. Patients should be advised not to drive or engage in other hazardous activities while pupils are dilated. Patients may experience sensitivity to light and should protect eyes in bright illumination during dilation. Parents should be warned not to get this preparation in their child's mouth and to wash their own hands and the child's hands following administration. Feeding intolerance may follow ophthalmic use of this product in infants. It is recommended that feeding be withheld for 4 hours after examination.

DRUG INTERACTIONS

Drug Interactions: Cyclopentolate may interfere with the ocular anti-hypertensive action of carbachol, pilocarpine, or ophthalmic cholinesterase inhibitors.

CARCINOGENESIS AND MUTAGENESIS AND IMPAIRMENT OF FERTILITY

Carcinogenesis, Mutagenesis, Impairment of Fertility: Studies in animals or humans have not been conducted to evaluate the carcinogenic potential of CYCLOGYL® (cyclopentolate hydrochloride ophthalmic solution, USP).

PREGNANCY

Pregnancy: Animal reproduction studies have not been conducted with cyclopentolate. It is also not known whether cyclopentolate can cause fetal harm when administered to a pregnant woman or can affect reproduction capacity. Cyclopentolate should be administered to a pregnant woman only if clearly needed.

LACTATION

Nursing Mothers: It is not known whether this drug is excreted in human milk. Because many drugs are excreted in human milk, caution should be exercised when cyclopentolate hydrochloride is administered to a nursing woman.

PEDIATRIC USE

Pediatric Use: Use of cyclopentolate has been associated with psychotic reactions and behavioral disturbances in pediatric patients. Increased susceptibility to cyclopentolate has been reported in infants, young children, and in children with spastic paralysis or brain damage. These disturbances include ataxia, incoherent speech, restlessness, hallucinations, hyperactivity, seizures, disorientation as to time and place, and failure to recognize people. Feeding intolerance and necrotizing enterocolitis (NEC) in preterm infants may follow ophthalmic use of this product. Cases of NEC have been reported in preterm infants following administration; however, causality has not been established. It is recommended that feeding be withheld for four (4) hours after examination. Observe infants closely for at least 30 minutes (see WARNINGS).

GERIATRIC USE

Geriatric Use: No overall differences in safety or effectiveness have been observed between elderly and younger patients.

ADVERSE REACTIONS:

Ocular: Increased intraocular pressure, burning, photophobia, blurred vision, irritation, hyperemia, conjunctivitis, blepharoconjunctivitis, punctate keratitis, synechiae have been reported.

Non-ocular: Use of cyclopentolate has been associated with psychotic reactions and behavioral disturbances, usually in children, especially with 2% concentration. These disturbances include ataxia, incoherent speech, restlessness, hallucinations, hyperactivity, seizures, disorientation as to time and place, and failure to recognize people. This drug produces reactions similar to those of other anticholinergic drugs, but the central nervous system manifestations as noted above are more common. Other toxic manifestations of anticholinergic drugs are skin rash, abdominal distention in infants, unusual drowsiness, tachycardia, hyperpyrexia, vasodilation, urinary retention, diminished gastrointestinal motility and decreased secretion in salivary and sweat glands, pharynx, bronchi and nasal passages. Severe manifestations of toxicity include coma, medullary paralysis and death.

OVERDOSAGE

OVERDOSAGE: Excessive dosage may produce behavioral disturbances, tachycardia, hyperpyrexia, hypertension, elevated intraocular pressure, vasodilation, urinary retention, diminished gastrointestinal motility and decreased secretion in salivary and sweat glands, pharynx, bronchi and nasal passages. Patients exhibiting signs of overdosage should receive supportive care and monitoring.

DOSAGE AND ADMINISTRATION: Adults: Instill one or two drops of 0.5%, 1% or 2% solution in the eye which may be repeated in five to ten minutes if necessary. Complete recovery usually occurs in 24 hours. Complete recovery from mydriasis in some individuals may require several days. Children: Instill one or two drops of 0.5%, 1% or 2% solution in the eye which may be repeated five to ten minutes later by a second application of 0.5% or 1% solution if necessary. Small Infants: A single instillation of one drop of 0.5% in the eye. To minimize absorption, apply pressure over the nasolacrimal sac for two to three minutes. Observe infant closely for at least 30 minutes following instillation. Individuals with heavily pigmented irides may require higher strengths.

HOW SUPPLIED

HOW SUPPLIED: In multiple-dose plastic DROP-TAINER® dispensers:

0.5% CYCLOGYL 1% CYCLOGYL 2% CYCLOGYL

15 mL NDC 0065-0395-15 2 mL NDC 0065-0396-02 2 mL NDC 0065-0397-02

5 mL NDC 0065-0396-05 5 mL NDC 0065-0397-05

15 mL NDC 0065-0396-15 15 mL NDC 0065-0397-15

Storage: Store at 8°C to 25°C (46°F to 77°F). After opening, Cyclogyl can be used until the expiration date on the bottle.

© 2021 Alcon Inc.
Revised: November 2021

ALCON LABORATORIES, INC.
Fort Worth, Texas 76134
300051372-1121

PRINCIPAL DISPLAY PANEL

NDC 0065-0395-15
Alcon
Cyclogyl® 0.5%
(cyclopentolate hydrochloride ophthalmic solution, USP)
15 mL Sterile
INGREDIENTS: Each mL contains: Active: cyclopentolate hydrochloride 0.5%. Preservative: benzalkonium chloride 0.01%. Inactives: boric acid, edetate disodium, potassium chloride, sodium carbonate and/or hydrochloric acid (to adjust pH), purified water. The pH range is between 3.0 and 5.5.
FOR TOPICAL OPHTHALMIC USE ONLY.
Rx Only
USUAL DOSAGE: Instill one or two drops in the eye which can be repeated in five to ten minutes. Read enclosed insert.
PRECAUTION: Do not touch dropper tip to any surface, as this may contaminate the solution.
STORAGE: Store at 8° to 25°C (46°-77°F). After opening Cyclogyl can be used until the expiration date on the bottle.
ALCON
ALCON LABORATORIES, INC.
Fort Worth, Texas 76134 USA
Product of Spain
300037981-0520
SN:
LOT:
EXP.:
GTIN: 00300650395151

NDC 0065-0395-15
Alcon
Cyclogyl® 0.5%
(cyclopentolate hydrochloride ophthalmic solution, USP)
Sterile 15 mL
Rx Only
INGREDIENTS: Each mL contains : Active: cyclopentolate hydrochloride 0.5%. Preservative: benzalkonium chloride 0.01%. Inactives: boric acid, edetate disodium, potassium chloride, sodium carbonate and/or hydrochloric acid (to adjust pH), purified water. The pH range is between 3.0 and 5.5.
PRECAUTION: Do not touch dropper tip to any surface, as this may contaminate the solution.
FOR TOPICAL OPHTHALMIC USE ONLY
USUAL DOSAGE: Instill one or two drops in the eye which can be repeated in five to ten minutes if necessary. Read enclosed insert.
STORAGE: Store at 8° to 25°C (46° to 77°F).
ALCON LABORATORIES, INC.
Fort Worth, Texas 76134 USA
Printed in USA
300037980-0520
LOT: EXP.:

NDC 0065-0396-05
Alcon
Cyclogyl® 1%
(cyclopentolate hydrochloride ophthalmic solution, USP)
5 mL Sterile
INGREDIENTS: Each mL contains : Active: cyclopentolate hydrochloride 1%. Preservative: benzalkonium chloride 0.01%. Inactives: boric acid, edetate disodium, potassium chloride, sodium carbonate and/or hydrochloric acid (to adjust pH), purified water. The pH range is between 3.0 and 5.5.
Rx Only
USUAL DOSAGE: Instill one or two drops in the eye which can be repeated in five to ten minutes if necessary. Read enclosed Insert.
PRECAUTION: Do not touch dropper tip to any surface, as this may contaminate the solution.
STORAGE: Store at 8° to 25°C (46° to 77°F). After opening, Cyclogyl can be used until the expiration date on the bottle.
FOR TOPICAL OPHTHALMIC USE ONLY.
Alcon
ALCON LABORATORIES, INC.
Fort Worth, Texas 76134 USA
Product of Spain
Printed in the USA
300037979 -0520
SN:
LOT:
EXP.:
GTIN: 00300650396059

NDC 0065-0396-05
Alcon
Cyclogyl® 1%
(cyclopentolate hydrochloride ophthalmic solution, USP)
Sterile 5 mL
Rx Only
INGREDIENTS: Each mL contains : Active: cyclopentolate hydrochloride 1%. Preservative: benzalkonium chloride 0.01%. Inactives: boric acid, edetate disodium, potassium chloride, sodium carbonate and/or hydrochloric acid (to adjust pH), purified water. The pH range is between 3.0 and 5.5.
PRECAUTION: Do not touch dropper tip to any surface, as this may contaminate the solution.
USUAL DOSAGE: Instill one or two drops in the eye which can be repeated in five to ten minutes if necessary. Read enclosed insert.
STORAGE: Store at 8° to 25°C (46° to 77°F).
ALCON LABORATORIES, INC.
Fort Worth, Texas 76134 USA Printed in USA
LOT EXP.:
300037978-0520

NDC 0065-0397-15
Alcon
Cyclogyl® 2%
(cyclopentolate hydrochloride ophthalmic solution, USP)
15 mL Sterile
Rx Only
USUAL DOSAGE: Instill one or two drops in the eye which can be repeated in five to ten minutes if necessary. Read enclosed insert.
PRECAUTION: Do not touch dropper tip to any surface, as this may contaminate the solution.
STORAGE: Store at 8° to 25°C (46° to 77°F). After opening, Cyclogyl can be used until the expiration date on the bottle.
INGREDIENTS: Each mL contains : Active: cyclopentolate hydrochloride 2%. Preservative: benzalkonium chloride 0.01%. Inactives: boric acid, edetate disodium, sodium carbonate and/or hydrochloric acid (to adjust pH), purified water. The pH range is between 3.0 and 5.5.
FOR TOPICAL OPHTHALMIC USE ONLY.
Alcon
ALCON LABORATORIES, INC.
Fort Worth, Texas 76134 USA
Product of Spain
Printed in USA
300037977-0520
SN:
LOT:
EXP.:
GTIN: 00300650397155

NDC 0065-0397-15
Alcon
Cyclogyl® 2%
(cyclopentolate hydrochloride ophthalmic solution, USP)
Sterile 15 mL
Rx Only INGREDIENTS: Each mL contains : Active: cyclopentolate hydrochloride 2%. Preservative: benzalkonium chloride 0.01%. Inactives: boric acid, edetate disodium, sodium carbonate and/or hydrochloric acid (to adjust pH), purified water. The pH range is between 3.0 and 5.5.
PRECAUTION: Do not touch dropper tip to any surface, as this may contaminate the solution.
USUAL DOSAGE: Instill one or two drops in the eye which can be repeated in five to ten minutes if necessary. Read enclosed Insert.
STORAGE: Store at 8° to 25°C (46° to 77°F).
ALCON LABORATORIES, INC.
Fort Worth, Texas 76134 USA
Printed in USA
LOT: EXP.:
300037975-0520